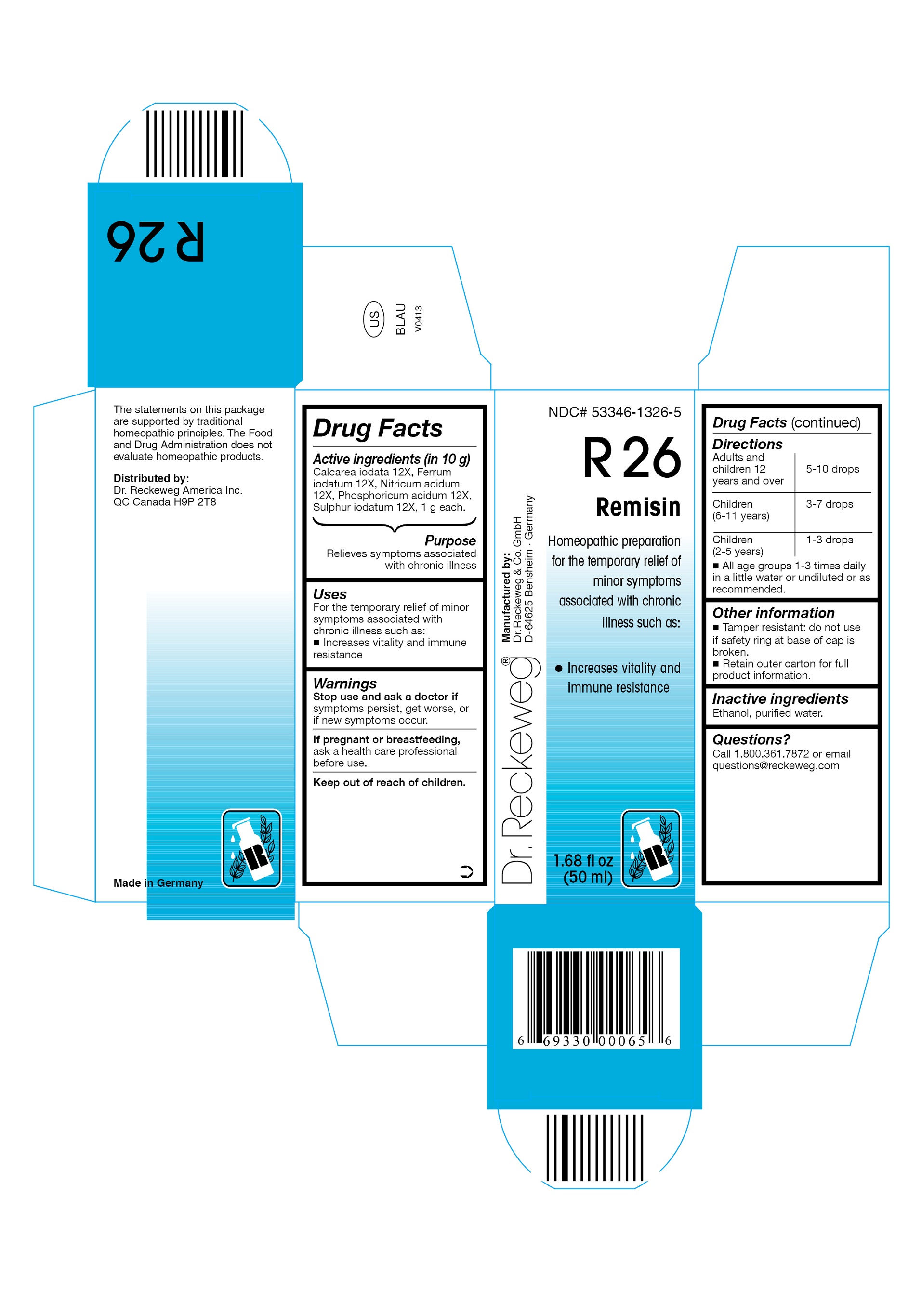 DRUG LABEL: DR. RECKEWEG R26 Remisin
NDC: 53346-1326 | Form: LIQUID
Manufacturer: PHARMAZEUTISCHE FABRIK DR. RECKEWEG & CO
Category: homeopathic | Type: HUMAN OTC DRUG LABEL
Date: 20130404

ACTIVE INGREDIENTS: CALCIUM IODIDE 12 [hp_X]/50 mL; FERROUS IODIDE 12 [hp_X]/50 mL; NITRIC ACID 12 [hp_X]/50 mL; PHOSPHORIC ACID 12 [hp_X]/50 mL; SULFUR IODIDE 12 [hp_X]/50 mL
INACTIVE INGREDIENTS: ALCOHOL; WATER

DR. RECKEWEG R26 Remisin

Active ingredients

Calcarea iodata 12X, Ferrum iodatum 12X, Nitricum acidum 12X, Phosphoricum acidum 12X, Sulphur iodatum 12X, 1 g each in 10 g.

Purpose

Relieves symptoms associated with chronic illness

Uses

For the temporary relief of minor symptoms associated with chronic illness such as:

- Increases vitality and immune resistance

Warnings

Stop use and ask a doctor if symptoms persist, get worse, or if new symptoms occur.

PREGNANCY OR BREAST FEEDING

If pregnant or breastfeeding, ask a health care professional before use.

Keep out of reach of children.

Directions

Adults and children ≥ 12 years 5-10 drops, children (6-11 years) 3-7 drops, children (2-5 years) 1-3 drops, all age groups 1-3 times daily in a little water or undiluted or as recommended.

Other information
Tamper resistant: do not use if safety ring at base of cap is broken.

Retain outer carton for full product information.

Inactive ingredients

Ethanol, purified water.

Questions?

Call 1-800-361-7872 or email questions@reckeweg.com

PACKAGE LABEL

NDC# 53346-1326-5

Dr. Reckeweg R26 Remisin

Homeopathic preparation for the temporary relief of minor symptoms associated with chronic illness such as:

- Increases vitality and immune resistance

Manufactured by:

Dr. Reckeweg Co. GmbH

D-64625 Bensheim

Germany

1.68 fl oz
(50 ml)